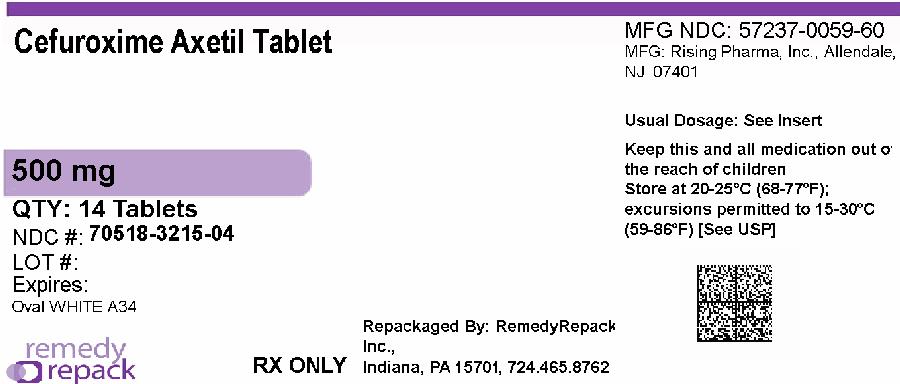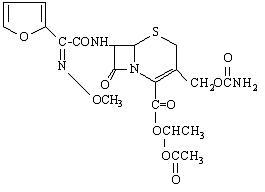 DRUG LABEL: Cefuroxime Axetil
NDC: 70518-3215 | Form: TABLET, FILM COATED
Manufacturer: REMEDYREPACK INC.
Category: prescription | Type: HUMAN PRESCRIPTION DRUG LABEL
Date: 20260213

ACTIVE INGREDIENTS: CEFUROXIME AXETIL 500 mg/1 1
INACTIVE INGREDIENTS: POLYETHYLENE GLYCOL 400; SILICON DIOXIDE; CROSCARMELLOSE SODIUM; HYDROGENATED COTTONSEED OIL; HYPROMELLOSE, UNSPECIFIED; MICROCRYSTALLINE CELLULOSE; SODIUM LAURYL SULFATE; TITANIUM DIOXIDE

HIGHLIGHTS OF PRESCRIBING INFORMATION

These highlights do not include all the information needed to use CEFUROXIME AXETIL TABLETS safely and effectively. See full prescribing information for CEFUROXIME AXETIL TABLETS.
CEFUROXIME AXETIL tablets, for oral use
Initial U.S. Approval: 1987

1 INDICATIONS AND USAGE

Cefuroxime axetil tablets are a cephalosporin antibacterial drug indicated for the treatment of the following infections due to susceptible bacteria: (1)

- Pharyngitis/tonsillitis (adults and pediatric patients) (1.1)
- Acute bacterial otitis media (pediatric patients) (1.2)
- Acute bacterial maxillary sinusitis (adults and pediatric patients) (1.3)
- Acute bacterial exacerbations of chronic bronchitis (adults and pediatric patients 13 years and older) (1.4)
- Uncomplicated skin and skin-structure infections (adults and pediatric patients 13 years and older) (1.5)
- Uncomplicated urinary tract infections (adults and pediatric patients 13 years and older) (1.6)
- Uncomplicated gonorrhea (adults and pediatric patients 13 years and older) (1.7)
- Early Lyme disease (adults and pediatric patients 13 years and older) (1.8)

To reduce the development of drug-resistant bacteria and maintain the effectiveness of cefuroxime axetil tablets and other antibacterial drugs, cefuroxime axetil tablets should be used only to treat or prevent infections that are proven or strongly suspected to be caused by bacteria.

2 DOSAGE AND ADMINISTRATION

- Tablets and oral suspension are not bioequivalent and are therefore not substitutable on a milligram-per-milligram basis. (2.1)
- Administer tablets with or without food. (2.2)
- Administer cefuroxime axetil tablets as described in the dosage guidelines. (2.2)
- Dosage adjustment is required for patients with impaired renal function. (2.5)

Adult Patientsand Pediatric Patients Dosage Guidelines for Cefuroxime Axetil Tablets
Infection | Dosage | Duration (Days)
Adultsand Adolescents (13 years and older)
Pharyngitis/tonsillitis (mild to moderate) | 250 mg every 12 hours | 10
Acute bacterial maxillary sinusitis (mild to moderate) | 250 mg every 12 hours | 10
Acute bacterial exacerbations of chronic bronchitis (mild to moderate) | 250 mg or 500 mg every 12 hours | 10
Uncomplicated skin and skin-structure infections | 250 mg or 500 mg every 12 hours | 10
Uncomplicated urinary tract infections | 250 mg every 12 hours | 7 to 10
Uncomplicated gonorrhea | 1,000 mg | single dose
Early Lyme disease | 500 mg every 12 hours | 20
Pediatric Patientsyounger than 13 years (who can swallow tablets whole)
Acute bacterial otitis media | 250 mg every 12 hours | 10
Acute bacterial maxillary sinusitis | 250 mg every 12 hours | 10

3 DOSAGE FORMS AND STRENGTHS

- Tablets: 500 mg (3)

4 CONTRAINDICATIONS

Known hypersensitivity (e.g., anaphylaxis) to cefuroxime axetil tablets or to other β-lactams (e.g., penicillins and cephalosporins). (4)

5 WARNINGS AND PRECAUTIONS

- Serious hypersensitivity (anaphylactic) reactions: In the event of a serious reaction, discontinue cefuroxime axetil and institute appropriate therapy. (5.1)
- Clostridioidesdifficile- associated diarrhea (CDAD): If diarrhea occurs, evaluate patients for CDAD. (5.2)

6 ADVERSE REACTIONS

The most common adverse reactions (≥3%) for cefuroxime axetil tablets are diarrhea, nausea/vomiting, Jarisch-Herxheimer reaction, and vaginitis (early Lyme disease). (6.1)
To report SUSPECTED ADVERSE REACTIONS, contact Rising Health, LLC at 1-833-395-6928 or FDA at 1-800-FDA-1088 or www.fda.gov/medwatch.

7 DRUG INTERACTIONS

- Drugs that reduce gastric acidity may lower the bioavailability of cefuroxime axetil. (7.1)
- Coadministration with probenecid increases systemic exposure to cefuroxime axetil and is therefore not recommended. (7.2)

FULL PRESCRIBING INFORMATION

1 INDICATIONS AND USAGE

1.1 Pharyngitis/Tonsillitis

Cefuroxime axetil tablets are indicated for the treatment of adult patients and pediatric patients (13 years and older) with mild-to-moderate pharyngitis/tonsillitis caused by susceptible strains of Streptococcus pyogenes.

Limitations of Use

- The efficacy of cefuroxime axetil tablets in the prevention of rheumatic fever was not established in clinical trials.
- The efficacy of cefuroxime axetil tablets in the treatment of penicillin-resistant strains of Streptococcus pyogeneshas not been demonstrated in clinical trials.

1.2 Acute Bacterial Otitis Media

Cefuroxime axetil tablets are indicated for the treatment of pediatric patients (who can swallow tablets whole) with acute bacterial otitis media caused by susceptible strains of Streptococcus pneumoniae, Haemophilus influenzae(including β-lactamase–producing strains), Moraxella catarrhalis(including β-lactamase–producing strains), or Streptococcus pyogenes.

1.3 Acute Bacterial Maxillary Sinusitis

Cefuroxime axetil tablets are indicated for the treatment of adult and pediatric patients (13 years and older) with mild-to-moderate acute bacterial maxillary sinusitis caused by susceptible strains of Streptococcus pneumoniaeor Haemophilus influenzae(non -β-lactamase–producing strains only).

Limitations of Use

The effectiveness of cefuroxime axetil tablets for sinus infections caused by β-lactamase–producing Haemophilus influenzaeor Moraxella catarrhalisin patients with acute bacterial maxillary sinusitis was not established due to insufficient numbers of these isolates in the clinical trials [see Clinical Studies (14.1)] .

1.4 Acute Bacterial Exacerbations of Chronic Bronchitis

Cefuroxime axetil tablets are indicated for the treatment of adult patients and pediatric patients (aged 13 and older) with mild-to-moderate acute bacterial exacerbations of chronic bronchitis caused by susceptible strains of Streptococcus pneumoniae, Haemophilus influenzae(β-lactamase–negative strains), or Haemophilus parainfluenzae(β-lactamase–negative strains).

1.5 Uncomplicated Skin and Skin-Structure Infections

Cefuroxime axetil tablets are indicated for the treatment of adult patients and pediatric patients (aged 13 and older) with uncomplicated skin and skin-structure infections caused by susceptible strains of Staphylococcus aureus(including β -lactamase–producing strains) or Streptococcus pyogenes.

1.6 Uncomplicated Urinary Tract Infections

Cefuroxime axetil tablets are indicated for the treatment of adult patients and pediatric patients (aged 13 and older) with uncomplicated urinary tract infections caused by susceptible strains of Escherichia colior Klebsiella pneumoniae.

1.7 Uncomplicated Gonorrhea

Cefuroxime axetil tablets are indicated for the treatment of adult patients and pediatric patients (aged 13 and older) with uncomplicated gonorrhea, urethral and endocervical, caused by penicillinase-producing and non-penicillinase–producing susceptible strains of Neisseria gonorrhoeaeand uncomplicated gonorrhea, rectal, in females, caused by non-penicillinase–producing susceptible strains of Neisseria gonorrhoeae.

1.8 Early Lyme Disease (erythema migrans)

Cefuroxime axetil tablets are indicated for the treatment of adult patients and pediatric patients (aged 13 and older) with early Lyme disease (erythema migrans) caused by susceptible strains of Borrelia burgdorferi.

1.10 Usage

To reduce the development of drug-resistant bacteria and maintain the effectiveness of cefuroxime axetil tablets and other antibacterial drugs, cefuroxime axetil tablets should be used only to treat or prevent infections that are proven or strongly suspected to be caused by susceptible bacteria. When culture and susceptibility information are available, they should be considered in selecting or modifying antibacterial therapy. In the absence of such data, local epidemiology and susceptibility patterns may contribute to the empiric selection of therapy.

2 DOSAGE AND ADMINISTRATION

2.1 Important Administration Instructions

- Cefuroxime axetil tablets and cefuroxime axetil for oral suspension are not bioequivalent and are therefore not substitutable on a milligram-per-milligram basis [see Clinical Pharmacology (12.3)] .
- Administer cefuroxime axetil tablets as described in the appropriate dosage guidelines [see Dosage and Administration (2.2)].
- Administer cefuroxime axetil tablets with or without food.
- Pediatric patients (aged 13 years and older) who cannot swallow the cefuroxime axetil tablets whole should receive cefuroxime axetil for oral suspension because the tablet has a strong, persistent bitter taste when crushed [see Dosage and Administration (2.2)].

2.2 Dosage for Cefuroxime Axetil Tablets

Administer cefuroxime axetil tablets as described in the dosage guidelines table below with or without food.

Table 1. Adult Patients and Pediatric Patients Dosage Guidelines for Cefuroxime Axetil Tablets
Infection | Dosage | Duration (Days)
Adults and Adolescents (13 years and older)
Pharyngitis/tonsillitis (mild to moderate) | 250 mg every 12 hours | 10
Acute bacterial maxillary sinusitis (mild to moderate) | 250 mg every 12 hours | 10
Acute bacterial exacerbations ofchronic bronchitis (mild to moderate) | 250 mg or 500 mg every 12 hours | 10a
Uncomplicated skin and skin-structure infections | 250 mg or 500 mg every 12 hours | 10
Uncomplicated urinary tract infections | 250 mg every 12 hours | 7 to 10
Uncomplicated gonorrhea | 1,000 mg | single dose
Early Lymedisease | 500 mg every 12 hours | 20
Pediatric Patients younger than 13 years (who can swallow tablets whole)b
Acute bacterial otitis media | 250 mg every 12 hours | 10
Acute bacterial maxillary sinusitis | 250 mg every 12 hours | 10
aThe safety and effectiveness of cefuroxime axetil tablets administered for less than 10 days in patients with acute exacerbations of chronic bronchitis have not been established.
bWhen crushed, the tablet has a strong, persistent bitter taste. Therefore, patients who cannot swallow the tablet whole should receive the oral suspension.

2.5 Dosage in Patients with Impaired Renal Function

A dosage interval adjustment is required for patients whose creatinine clearance is less than 30 mL/min, as listed in Table 4 below, because cefuroxime is eliminated primarily by the kidney [see Clinical Pharmacology (12.3)].

Table 4. Dosing in Adults with Renal Impairment
Creatinine Clearance (mL/min) | Recommended Dosage
≥30 | No dosage adjustment
10 to <30 | Standard individual dose given every 24 hours
<10 (without hemodialysis) | Standard individual dose given every 48 hours
Hemodialysis | A single additional standard dose should be given at the end of each dialysis

3 DOSAGE FORMS AND STRENGTHS

Cefuroxime Axetil Tablets USP, 500 mg of cefuroxime (as cefuroxime axetil), are white to off-white, film-coated, capsule shaped tablets with ‘A34’ debossed on one side and plain on the other side.

4 CONTRAINDICATIONS

Cefuroxime axetil tablets are contraindicated in patients with a known hypersensitivity (e.g., anaphylaxis) to cefuroxime axetil tablets or to other β-lactam antibacterial drugs (e.g., penicillins and cephalosporins).

5 WARNINGS AND PRECAUTIONS

5.1 Anaphylactic Reactions

Serious and occasionally fatal hypersensitivity (anaphylactic) reactions have been reported in patients on β-lactam antibacterials, including cefuroxime axetil [see Adverse Reactions (6.2)] . These reactions are more likely to occur in individuals with a history of β-lactam hypersensitivity and/or a history of sensitivity to multiple allergens. There have been reports of individuals with a history of penicillin hypersensitivity who have experienced severe reactions when treated with cephalosporins. Cefuroxime axetil is contraindicated in patients with a known hypersensitivity to cefuroxime axetil or other β-lactam antibacterial drugs [see Contraindications (4)] . Before initiating therapy with cefuroxime axetil, inquire about previous hypersensitivity reactions to penicillins, cephalosporins, or other allergens. If an allergic reaction occurs, discontinue cefuroxime axetil and institute appropriate therapy.

5.2 Clostridioides difficile-Associated Diarrhea

Clostridioidesdifficile- associated diarrhea (CDAD) has been reported with use of nearly all antibacterial agents, including cefuroxime axetil, and may range in severity from mild diarrhea to fatal colitis. Treatment with antibacterial agents alters the normal flora of the colon leading to overgrowth of C. difficile.
C. difficile produces toxins A and B which contribute to the development of CDAD. Hypertoxin-producing strains of C. difficilecause increased morbidity and mortality, as these infections can be refractory to antimicrobial therapy and may require colectomy. CDAD must be considered in all patients who present with diarrhea following antibiotic use. Careful medical history is necessary since CDAD has been reported to occur over 2 months after the administration of antibacterial agents.
If CDAD is suspected or confirmed, ongoing antibiotic use not directed against C. difficilemay need to be discontinued. Appropriate fluid and electrolyte management, protein supplementation, antibiotic treatment of C. difficile, and surgical evaluation should be instituted as clinically indicated.

5.3 Potential for Microbial Overgrowth

The possibility of superinfections with fungal or bacterial pathogens should be considered during therapy.

5.4 Development of Drug-Resistant Bacteria

Prescribing cefuroxime axetil either in the absence of a proven or strongly suspected bacterial infection or a prophylactic indication is unlikely to provide benefit to the patient and increases the risk of the development of drug-resistant bacteria.

5.6 Interference with Glucose Tests

A false-positive result for glucose in the urine may occur with copper reduction tests, and a false-negative result for blood/plasma glucose may occur with ferricyanide tests in subjects receiving cefuroxime axetil [see Drug Interactions (7.3)] .

6 ADVERSE REACTIONS

The following serious and otherwise important adverse reaction is described in greater detail in the Warnings and Precautions section of the label:

Anaphylactic Reactions [see Warnings and Precautions (5.1)].

6.1 Clinical Trials Experience

Because clinical trials are conducted under widely varying conditions, adverse reaction rates observed in the clinical trials of a drug cannot be directly compared with rates in the clinical trials of another drug and may not reflect the rates observed in practice.

Tablets

Multiple-Dose Dosing Regimens with 7 to 10 Days’ Duration: In multiple-dose clinical trials, 912 subjects were treated with cefuroxime axetil (125 to 500 mg twice daily). It is noted that 125 mg twice daily is not an approved dosage. Twenty (2.2%) subjects discontinued medication due to adverse reactions. Seventeen (85%) of the 20 subjects who discontinued therapy did so because of gastrointestinal disturbances, including diarrhea, nausea, vomiting, and abdominal pain. The percentage of subjects treated with cefuroxime axetil who discontinued study drug because of adverse reactions was similar at daily doses of 1,000, 500, and 250 mg (2.3%, 2.1%, and 2.2%, respectively). However, the incidence of gastrointestinal adverse reactions increased with the higher recommended doses.

The adverse reactions in Table 5 are for subjects (n = 912) treated with cefuroxime axetil in multiple-dose clinical trials.

Table 5. Adverse Reactions (≥1%) after Multiple-Dose Regimens with Cefuroxime Axetil Tablets
Adverse Reaction | Cefuroxime Axetil (n = 912)
Blood and lymphatic system disorders
Eosinophilia | 1%
Gastrointestinal disorders
Diarrhea | 4%
Nausea/Vomiting | 3%
Investigations
Transient elevation in AST | 2%
Transient elevation in ALT | 2%
Transient elevation in LDH | 1%

The following adverse reactions occurred in less than 1% but greater than 0.1% of subjects (n = 912) treated with cefuroxime axetil in multiple-dose clinical trials.
Immune System Disorders: Hives, swollen tongue.
Metabolism and Nutrition Disorders:Anorexia.
Nervous System Disorders:Headache.
Cardiac Disorders: Chest pain.
Respiratory Disorders: Shortness of breath.
Gastrointestinal Disorders: Abdominal pain, abdominal cramps, flatulence, indigestion, mouth ulcers.
Skin and Subcutaneous Tissue Disorders: Rash, itch.
Renal and Urinary Disorders: Dysuria.
Reproductive System and Breast Disorders: Vaginitis, vulvar itch.
General Disorders and Administration Site Conditions: Chills, sleepiness, thirst.
Investigations: Positive Coombs’ test.
Early Lyme Disease with 20-Day Regimen: Two multicenter trials assessed cefuroxime axetil 500 mg twice daily for 20 days. The most common drug-related adverse experiences were diarrhea (10.6%), Jarisch-Herxheimer reaction (5.6%), and vaginitis (5.4%). Other adverse experiences occurred with frequencies comparable to those reported with 7 to 10 days’ dosing.
Single-Dose Regimen for Uncomplicated Gonorrhea: In clinical trials using a single 1,000 mg dose of cefuroxime axetil, 1,061 subjects were treated for uncomplicated gonorrhea.
The adverse reactions in Table 6 were for subjects treated with a single dose of 1,000 mg cefuroxime axetil in U.S. clinical trials.

Table 6. Adverse Reactions (≥1%) after Single-Dose Regimen with 1,000 mg Cefuroxime Axetil Tablets for Uncomplicated Gonorrhea
Adverse Reaction | Cefuroxime Axetil (n = 1,061)
Gastrointestinal disorders
Nausea/Vomiting | 7%
Diarrhea | 4%

The following adverse reactions occurred in less than 1% but greater than 0.1% of subjects (n = 1,061) treated with a single dose of cefuroxime axetil 1,000 mg for uncomplicated gonorrhea in U.S. clinical trials.
Infections and Infestations: Vaginal candidiasis.
Nervous System Disorders: Headache, dizziness, somnolence.
Cardiac Disorders: Tightness/pain in chest, tachycardia.
Gastrointestinal Disorders: Abdominal pain, dyspepsia.
Skin and Subcutaneous Tissue Disorders: Erythema, rash, pruritus.
Musculoskeletal and Connective Tissue Disorders: Muscle cramps, muscle stiffness, muscle spasm of neck, lockjaw-type reaction.
Renal and Urinary Disorders: Bleeding/pain in urethra, kidney pain.
Reproductive System and Breast Disorders: Vaginal itch, vaginal discharge.

6.2 Postmarketing Experience

The following adverse reactions have been identified during post-approval use of cefuroxime axetil. Because these reactions are reported voluntarily from a population of uncertain size, it is not always possible to reliably estimate their frequency or establish a causal relationship to drug exposure.

Blood and Lymphatic System Disorders

Hemolytic anemia, leukopenia, pancytopenia, thrombocytopenia.

Gastrointestinal Disorders

Pseudomembranous colitis [see Warnings and Precautions (5.2)] .

Hepatobiliary Disorders

Hepatic impairment including hepatitis and cholestasis, jaundice.

Immune System Disorders

Anaphylaxis, serum sickness-like reaction, acute myocardial ischemia with or without myocardial infarction may occur as part of an allergic reaction.
Investigations

Increased prothrombin time.

Nervous System Disorders

Seizure, encephalopathy.

Renal and Urinary Disorders

Renal dysfunction.

Skin and Subcutaneous Tissue Disorders

Angioedema, erythema multiforme, Stevens-Johnson syndrome, toxic epidermal necrolysis, urticaria.

7 DRUG INTERACTIONS

7.1 Drugs that Reduce Gastric Acidity

Drugs that reduce gastric acidity may result in a lower bioavailability of cefuroxime axetil compared with administration in the fasting state. Administration of drugs that reduce gastric acidity may negate the food effect of increased absorption of cefuroxime axetil when administered in the postprandial state. Administer cefuroxime axetil at least 1 hour before or 2 hours after administration of short-acting antacids. Histamine-2 (H2) antagonists and proton pump inhibitors should be avoided.

7.2 Probenecid

Concomitant administration of probenecid with cefuroxime axetil tablets increases serum concentrations of cefuroxime [see Clinical Pharmacology (12.3)]. Coadministration of probenecid with cefuroxime axetil is not recommended.

7.3 Drug/Laboratory Test Interactions

A false-positive reaction for glucose in the urine may occur with copper reduction tests (e.g., Benedict's or Fehling's solution), but not with enzyme-based tests for glycosuria. As a false-negative result may occur in the ferricyanide test, it is recommended that either the glucose oxidase or hexokinase method be used to determine blood/plasma glucose levels in patients receiving cefuroxime axetil. The presence of cefuroxime does not interfere with the assay of serum and urine creatinine by the alkaline picrate method.

8 USE IN SPECIFIC POPULATIONS

8.1 Pregnancy

Risk Summary

Available data from published epidemiologic studies, case series, and case reports over several decades with cephalosporin use, including cefuroxime axetil, in pregnant women have not established drug-associated risks of major birth defects, miscarriage, or adverse maternal or fetal outcomes (see Data).
In studies in pregnant mice and rats administered oral cefuroxime axetil during organogenesis at 14 and 9 times the maximum recommended human dose (MRHD) based on body surface area, respectively, there were no adverse developmental outcomes (see Data).
The estimated background risk of major birth defects and miscarriage for the indicated populations are unknown. All pregnancies have a background risk of birth defects, loss, or other adverse outcomes. In the U.S. general population, the estimated background risk of major birth defects and miscarriage in clinically recognized pregnancies is 2% to 4% and 15% to 20%, respectively.
Clinical Considerations
Disease-Associated Maternal and/or Embryo/Fetal Risk: Maternal gonorrhea may be associated with preterm birth, low neonatal birth weight, chorioamnionitis, intrauterine growth restriction, small for gestational age, and premature rupture of membranes. Perinatal transmission of gonorrhea to the offspring can result in infant blindness, joint infections, and bloodstream infections.
Data
Human Data: While available studies cannot definitively establish the absence of risk, published data from epidemiologic studies, case series, and case reports over several decades have not identified an association with cephalosporin use (including cefuroxime axetil) during pregnancy and major birth defects, miscarriage, or other adverse maternal or fetal outcomes. Available studies have methodologic limitations, including small sample size, retrospective data collection, and inconsistent comparator groups.
Animal Data: Studies performed with oral cefuroxime axetil administered to pregnant mice during organogenesis (Gestation Days 7 through 16) at doses up to 3,200 mg/kg/day (14 times the MRHD based on body surface area); and in rats dosed during organogenesis and lactation (Gestation Days 7 through 16 and Gestation Days 17 through Lactation Day 21, respectively) at doses up to 1,000 mg/kg/day (9 times the MRHD based on body surface area) have revealed no adverse developmental outcomes.

8.2 Lactation

Risk Summary

Based on several published case reports describing multiple lactating women who received cefuroxime via intravenous, intramuscular, and oral routes, cefuroxime is present in human milk. The highest maternal milk concentration described occurred in lactating women 8 hours after an intramuscular administration of cefuroxime 750 mg. Allowing for an infant milk consumption of 150 mL/kg/day, the estimated breastfed infant dose would be less than 1% of the adult dose .No data are available on the effects of the drug on the breastfed infant or the effects of the drug on milk production. The developmental and health benefits of breastfeeding should be considered along with the mother’s clinical need for cefuroxime and any potential adverse effects on the breastfed infant from cefuroxime or from the underlying maternal condition.

8.4 Pediatric Use

The safety and effectiveness of cefuroxime axetil have been established for pediatric patients aged 3 months to 12 years for acute bacterial maxillary sinusitis based upon its approval in adults. Use of cefuroxime axetil in pediatric patients is supported by pharmacokinetic and safety data in adults and pediatric patients, and by clinical and microbiological data from adequate and well-controlled trials of the treatment of acute bacterial maxillary sinusitis in adults and of acute otitis media with effusion in pediatric patients. It is also supported by postmarketing adverse events surveillance [see Indications and Usage (1), Dosage and Administration (2), Adverse Reactions (6), Clinical Pharmacology (12.3)].

8.5 Geriatric Use

Of the total number of subjects who received cefuroxime axetil in 20 clinical trials, 375 were aged 65 and older while 151 were aged 75 and older. No overall differences in safety or effectiveness were observed between these subjects and younger adult subjects. Reported clinical experience has not identified differences in responses between the elderly and younger adult patients, but greater sensitivity of some older individuals cannot be ruled out.

Cefuroxime is substantially excreted by the kidney, and the risk of adverse reactions may be greater in patients with impaired renal function. Because elderly patients are more likely to have decreased renal function, care should be taken in dose selection, and it may be useful to monitor renal function.

8.6 Renal Impairment

Reducing the dosage of cefuroxime axetil is recommended for adult patients with severe renal impairment (creatinine clearance <30 mL/min) [see Dosage and Administration (2.5), Clinical Pharmacology (12.3)] .

10 OVERDOSAGE

Overdosage of cephalosporins can cause cerebral irritation leading to convulsions or encephalopathy. Serum levels of cefuroxime can be reduced by hemodialysis and peritoneal dialysis.

11 DESCRIPTION

Cefuroxime axetil tablets, USP contain cefuroxime as cefuroxime axetil. Cefuroxime axetil is a semisynthetic, cephalosporin antibacterial drug for oral administration.

The chemical name of cefuroxime axetil (1-(acetyloxy) ethyl ester of cefuroxime) is (RS)-1-hydroxyethyl (6 R,7 R)-7-[2-(2-furyl)glyoxyl-amido]-3-(hydroxymethyl)-8-oxo-5-thia-1-azabicyclo[4.2.0]-oct-2-ene-2-carboxylate, 7^2-(Z)-(O-methyl-oxime), 1-acetate 3-carbamate. Its molecular formula is C20H22N4O10S, and it has a molecular weight of 510.48.

Cefuroxime axetil is in the amorphous form and has the following structural formula:
Tablets are film-coated and contain the equivalent of 250 mg or 500 mg of cefuroxime as cefuroxime axetil USP. Tablets contain the inactive ingredients colloidal silicon dioxide, croscarmellose sodium, hydrogenated vegetable oil, hypromellose, microcrystalline cellulose, polyethylene glycol, sodium lauryl sulfate, and titanium dioxide.

12 CLINICAL PHARMACOLOGY

12.1 Mechanism of Action

Cefuroxime axetil is an antibacterial drug [see Microbiology (12.4)].

12.3 Pharmacokinetics

Absorption

After oral administration, cefuroxime axetil is absorbed from the gastrointestinal tract and rapidly hydrolyzed by nonspecific esterases in the intestinal mucosa and blood to cefuroxime. Serum pharmacokinetic parameters for cefuroxime following administration of cefuroxime axetil tablets to adults are shown in Table 8.

Table 8. Pharmacokinetics of Cefuroxime Administered in the Postprandial State as Cefuroxime Axetil Tablets to Adultsa
Doseb(Cefuroxime Equivalent) | Peak Plasma Concentration (mcg/mL) | Time of Peak Plasma Concentration (h) | Mean Elimination Half-life (h) | AUC (mcg·h/mL)
125 mg | 2.1 | 2.2 | 1.2 | 6.7
250 mg | 4.1 | 2.5 | 1.2 | 12.9
500 mg | 7 | 3 | 1.2 | 27.4
1,000 mg | 13.6 | 2.5 | 1.3 | 50
a Mean values of 12 healthy adult volunteers.
b Drug administered immediately after a meal.

Effect of Food:Absorption of the tablet is greater when taken after food (absolute bioavailability increases from 37% to 52%). Despite this difference in absorption, the clinical and bacteriologic responses of subjects were independent of food intake at the time of tablet administration in 2 trials where this was assessed.
Lack of Bioequivalence: Oral suspension was not bioequivalent to tablets when tested in healthy adults. The tablet and oral suspension formulations are NOT substitutable on a milligram-per-milligram basis. The area under the curve for the suspension averaged 91% of that for the tablet, and the peak plasma concentration for the suspension averaged 71% of the peak plasma concentration of the tablets. Therefore, the safety and effectiveness of both the tablet and oral suspension formulations were established in separate clinical trials.
Distribution
Cefuroxime is distributed throughout the extracellular fluids. Approximately 50% of serum cefuroxime is bound to protein.
Metabolism
The axetil moiety is metabolized to acetaldehyde and acetic acid.
Excretion
Cefuroxime is excreted unchanged in the urine; in adults, approximately 50% of the administered dose is recovered in the urine within 12 hours. The pharmacokinetics of cefuroxime in pediatric subjects have not been studied. Until further data are available, the renal elimination of cefuroxime axetil established in adults should not be extrapolated to pediatric subjects.
Specific Populations
Patients with Renal Impairment: In a trial of 28 adults with normal renal function or severe renal impairment (creatinine clearance <30 mL/min), the elimination half-life was prolonged in relation to severity of renal impairment. Prolongation of the dosage interval is recommended in adult patients with creatinine clearance <30 mL/min [see Dosage and Administration (2.5)] .
Geriatric Patients: In a trial of 20 elderly subjects (mean age = 83.9 years) having a mean creatinine clearance of 34.9 mL/min, the mean serum elimination half-life was prolonged to 3.5 hours; however, despite the lower elimination of cefuroxime in geriatric patients, dosage adjustment based on age is not necessary [see Use in Specific Populations (8.5)] .
Drug Interaction Studies
Concomitant administration of probenecid with cefuroxime axetil tablets increases the cefuroxime area under the serum concentration versus time curve and maximum serum concentration by 50% and 21%, respectively [see Drug Interactions (7.2)] .

12.4 Microbiology

Mechanism of Action

Cefuroxime axetil is a bactericidal agent that acts by inhibition of bacterial cell wall synthesis. Cefuroxime axetil has activity in the presence of some β-lactamases, both penicillinases and cephalosporinases, of gram-negative and gram-positive bacteria.

Resistance

Resistance to cefuroxime axetil is primarily through hydrolysis by β-lactamase, alteration of penicillin-binding proteins (PBPs), decreased permeability, and the presence of bacterial efflux pumps.

Susceptibility to cefuroxime axetil will vary with geography and time; local susceptibility data should be consulted, if available. Beta-lactamase -negative, ampicillin-resistant (BLNAR) isolates of H. influenzaeshould be considered resistant to cefuroxime axetil.
Antimicrobial Activity
Cefuroxime axetil has been shown to be active against most isolates of the following bacteria, both in vitroand in clinical infections [see Indications and Usage (1)] :

Aerobic Bacteria:

Gram-positive bacteria

- Staphylococcus aureus(methicillin-susceptible isolates only)
- Streptococcus pneumoniae
- Streptococcus pyogenes

Gram-negative bacteria

- Escherichia colia
- Klebsiella pneumoniaea
- Haemophilus influenzae
- Haemophilus parainfluenzae
- Moraxella catarrhalis
- Neisseria gonorrhoeae

a Most extended spectrum β-lactamase (ESBL) -producing and carbapenemase-producing isolates are resistant to cefuroxime axetil.

Spirochetes

- Borrelia burgdorferi

The following in vitrodata are available, but their clinical significance is unknown. At least 90 percent of the following bacteria exhibit an in vitrominimum inhibitory concentration (MIC) less than or equal to the susceptible breakpoint for cefuroxime against isolates of similar genus or organism group. However, the efficacy of cefuroxime axetil in treating clinical infections caused by these bacteria has not been established in adequate and well-controlled clinical trials.

Aerobic Bacteria:

Gram-positive bacteria

- Staphylococcus epidermidis(methicillin-susceptible isolates only)
- Staphylococcus saprophyticus(methicillin-susceptible isolates only)
- Streptococcus agalactiae

Gram-negative bacteria

- Morganella morganii
- Proteus inconstans
- Proteus mirabilis
- Providencia rettgeri

Anaerobic Bacteria:

Gram-positive bacteria

- Peptococcus niger

Susceptibility Testing

For specific information regarding susceptibility test interpretive criteria and associated test methods and quality control standards recognized by FDA for this drug, please see: https://www.fda.gov/STIC.

13 NONCLINICAL TOXICOLOGY

13.1 Carcinogenesis, Mutagenesis, Impairment of Fertility

Although lifetime studies in animals have not been performed to evaluate carcinogenic potential, no mutagenic activity was found for cefuroxime axetil in a battery of bacterial mutation tests. Positive results were obtained in an in vitrochromosome aberration assay; however, negative results were found in an in vivomicronucleus test at doses up to 1.5 g/kg. Fertility studies in rats (males dosed for 70 days prior to and through mating; females dosed 21 days prior to mating through lactation) at doses up to 1,000 mg/kg/day (9 times the MRHD based on body surface area) have revealed no adverse effects on fertility.

14 CLINICAL STUDIES

14.1 Acute Bacterial Maxillary Sinusitis

One adequate and well-controlled trial was performed in subjects with acute bacterial maxillary sinusitis. In this trial, each subject had a maxillary sinus aspirate collected by sinus puncture before treatment was initiated for presumptive acute bacterial sinusitis. All subjects had radiographic and clinical evidence of acute maxillary sinusitis. In the trial, the clinical effectiveness of cefuroxime axetil in treating acute maxillary sinusitis was comparable to an oral antimicrobial agent containing a specific β-lactamase inhibitor. However, microbiology data demonstrated cefuroxime axetil to be effective in treating acute bacterial maxillary sinusitis due only to Streptococcus pneumoniaeor non-β-lactamase–producing Haemophilus influenzae. Insufficient numbers of β-lactamase–producing Haemophilus influenzaeand Moraxella catarrhalisisolates were obtained in this trial to adequately evaluate the effectiveness of cefuroxime axetil in treating acute bacterial maxillary sinusitis due to these 2 organisms.

This trial randomized 317 adult subjects, 132 subjects in the U.S. and 185 subjects in South America. Table 10 shows the results of the intent-to-treat analysis.

Table 10. Clinical Effectiveness of Cefuroxime Axetil Tablets in the Treatment of Acute Bacterial Maxillary Sinusitis
 | U.S. Subjectsa |  | South American Subjectsb
 | Cefuroxime Axetil 250 mg Twice Daily (n = 49) | Controlc (n = 43) | Cefuroxime Axetil 250 mg Twice Daily (n = 49) | Controlc (n = 43)
Clinical success (cure + improvement) | 65% | 53% | 77% | 74%
Clinical cure | 53% | 44% | 72% | 64%
Clinical improvement | 12% | 9% | 5% | 10%
a95% confidence interval around the success difference [-0.08, +0.32].
b95% confidence interval around the success difference [-0.1, +0.16].
cControl was an antibacterial drug containing a β-lactamase inhibitor.

In this trial and in a supporting maxillary puncture trial, 15 evaluable subjects had non-β-lactamase–producing Haemophilus influenzaeas the identified pathogen. Of these, 67% (10/15) had this pathogen eradicated. Eighteen (18) evaluable subjects had Streptococcus pneumoniaeas the identified pathogen. Of these, 83% (15/18) had this pathogen eradicated.

14.2 Early Lyme Disease

Two adequate and well-controlled trials were performed in subjects with early Lyme disease. All subjects presented with physician-documented erythema migrans, with or without systemic manifestations of infection. Subjects were assessed at 1 month posttreatment for success in treating early Lyme disease (Part I) and at 1 year posttreatment for success in preventing the progression to the sequelae of late Lyme disease (Part II).

A total of 355 adult subjects (181 treated with cefuroxime axetil and 174 treated with doxycycline) were randomized in the 2 trials, with diagnosis of early Lyme disease confirmed in 79% (281/355). The clinical diagnosis of early Lyme disease in these subjects was validated by 1) blinded expert reading of photographs, when available, of the pretreatment erythema migrans skin lesion, and 2) serologic confirmation (using enzyme-linked immunosorbent assay [ELISA] and immunoblot assay [“Western” blot]) of the presence of antibodies specific to Borrelia burgdorferi, the etiologic agent of Lyme disease. The efficacy data in Table 11 are specific to this “validated” patient subset, while the safety data below reflect the entire patient population for the 2 trials. Clinical data for evaluable subjects in the “validated” patient subset are shown in Table 11.

Table 11. Clinical Effectiveness of Cefuroxime Axetil Tablets Compared with Doxycycline in the Treatment of Early Lyme Disease
 | Part I (1 Month after 20 Days of Treatment)a |  | Part II (1 Year after 20 Days of Treatment)b
 | Cefuroxime Axetil 500 mg Twice Daily (n = 125) | Doxycycline 100 mg 3 Times Daily (n = 108) | Cefuroxime Axetil 500 mg Twice Daily (n = 105c) | Doxycycline 100 mg 3 Times Daily (n = 83c)
Satisfactory clinical outcomed | 91% | 93% | 84% | 87%
Clinical cure/success | 72% | 73% | 73% | 73%
Clinical improvement | 19% | 19% | 10% | 13%
a95% confidence interval around the satisfactory difference for Part I (-0.08, +0.05).
b95% confidence interval around the satisfactory difference for Part II (-0.13, +0.07).
cn’s include subjects assessed as unsatisfactory clinical outcomes (failure + recurrence) in Part I (cefuroxime axetil - 11 [5 failure, 6 recurrence]; doxycycline - 8 [6 failure, 2 recurrence]).
dSatisfactory clinical outcome includes cure + improvement (Part I) and success + improvement (Part II).

Cefuroxime axetil and doxycycline were effective in prevention of the development of sequelae of late Lyme disease.

While the incidence of drug-related gastrointestinal adverse reactions was similar in the 2 treatment groups (cefuroxime axetil - 13%; doxycycline - 11%), the incidence of drug-related diarrhea was higher in the cefuroxime axetil arm versus the doxycycline arm (11% versus 3%, respectively).

16 HOW SUPPLIED/STORAGE AND HANDLING

Cefuroxime Axetil Tablets USP, 500 mg of cefuroxime (as cefuroxime axetil), are white to off-white, film-coated, capsule shaped tablets with ‘A34’ debossed on one side and plain on the other side.

NDC: 70518-3215-00

NDC: 70518-3215-01

NDC: 70518-3215-02

NDC: 70518-3215-03

NDC: 70518-3215-04

PACKAGING: 30 in 1 BLISTER PACK

PACKAGING: 20 in 1 BOTTLE PLASTIC

PACKAGING: 30 in 1 BOTTLE PLASTIC

PACKAGING: 20 in 1 BOTTLE PLASTIC

PACKAGING: 14 in 1 BOTTLE PLASTIC

Store at 20° to 25°C (68° to 77°F); excursions permitted to 15° to 30°C (59° to 86°F) [see USP Controlled Room Temperature]. Replace cap securely after each opening.

Repackaged and Distributed By:

Remedy Repack, Inc.

625 Kolter Dr. Suite #4 Indiana, PA 1-724-465-8762

17 PATIENT COUNSELING INFORMATION

Allergic Reactions
Inform patients that cefuroxime axetil is a cephalosporin that can cause allergic reactions in some individuals [see Warnings and Precautions (5.1)] .
Clostridioidesdifficile -Associated Diarrhea
Inform patients that diarrhea is a common problem caused by antibacterials, and it usually ends when the antibacterial is discontinued. Sometimes after starting treatment with antibacterials, patients can develop watery and bloody stools (with or without stomach cramps and fever) even as late as 2 or more months after having taken their last dose of the antibacterial. If this occurs, advise patients to contact their physician as soon as possible.
Crushing Tablets
Instruct patients to swallow the tablet whole, without crushing the tablet. Patients who cannot swallow the tablet whole should receive the oral suspension.

Drug Resistance
Inform patients that antibacterial drugs, including cefuroxime axetil, should only be used to treat bacterial infections. They do not treat viral infections (e.g., the common cold). When cefuroxime axetil is prescribed to treat a bacterial infection, inform patients that although it is common to feel better early in the course of therapy, the medication should be taken exactly as directed. Skipping doses or not completing the full course of therapy may: (1) decrease the effectiveness of the immediate treatment, and (2) increase the likelihood that bacteria will develop resistance and will not be treatable by cefuroxime axetil or other antibacterial drugs in the future.

Repackaged By / Distributed By: RemedyRepack Inc.

625 Kolter Drive, Indiana, PA 15701

(724) 465-8762

PRINCIPAL DISPLAY PANEL

DRUG: Cefuroxime Axetil

GENERIC: Cefuroxime Axetil

DOSAGE: TABLET, FILM COATED

ADMINSTRATION: ORAL

NDC: 70518-3215-0

NDC: 70518-3215-1

NDC: 70518-3215-2

NDC: 70518-3215-3

NDC: 70518-3215-4

COLOR: white

SHAPE: OVAL

SCORE: No score

SIZE: 20 mm

IMPRINT: A34

PACKAGING: 30 in 1 BLISTER PACK

PACKAGING: 20 in 1 BOTTLE PLASTIC

PACKAGING: 30 in 1 BOTTLE PLASTIC

PACKAGING: 20 in 1 BOTTLE PLASTIC

PACKAGING: 14 in 1 BOTTLE PLASTIC

ACTIVE INGREDIENT(S):

- CEFUROXIME AXETIL 500mg in 1

INACTIVE INGREDIENT(S):

- SILICON DIOXIDE
- CROSCARMELLOSE SODIUM
- HYDROGENATED COTTONSEED OIL
- HYPROMELLOSE, UNSPECIFIED
- MICROCRYSTALLINE CELLULOSE
- POLYETHYLENE GLYCOL 400
- SODIUM LAURYL SULFATE
- TITANIUM DIOXIDE